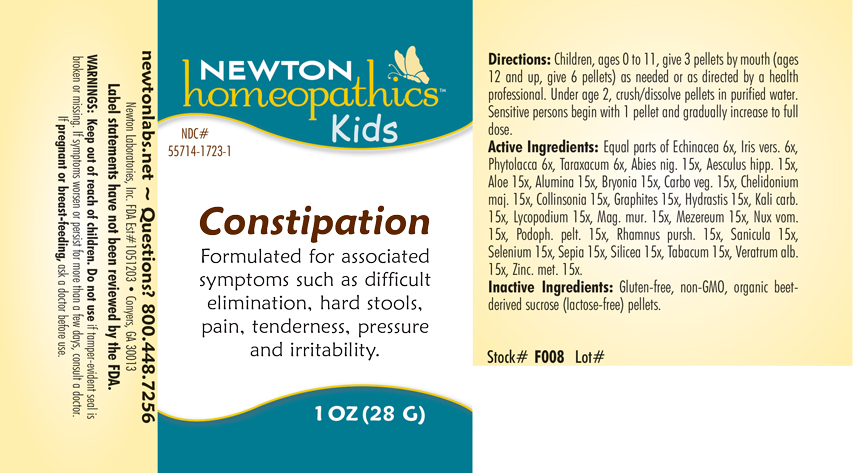 DRUG LABEL: Constipation
NDC: 55714-1723 | Form: PELLET
Manufacturer: Newton Laboratories, Inc.
Category: homeopathic | Type: HUMAN OTC DRUG LABEL
Date: 20250128

ACTIVE INGREDIENTS: ZINC 15 [hp_X]/1 g; ECHINACEA, UNSPECIFIED 6 [hp_X]/1 g; COLLINSONIA CANADENSIS ROOT 15 [hp_X]/1 g; PHYTOLACCA AMERICANA ROOT 6 [hp_X]/1 g; TARAXACUM OFFICINALE 6 [hp_X]/1 g; PICEA MARIANA RESIN 15 [hp_X]/1 g; HORSE CHESTNUT 15 [hp_X]/1 g; ALOE 15 [hp_X]/1 g; ALUMINUM OXIDE 15 [hp_X]/1 g; BRYONIA ALBA ROOT 15 [hp_X]/1 g; ACTIVATED CHARCOAL 15 [hp_X]/1 g; CHELIDONIUM MAJUS 15 [hp_X]/1 g; GOLDENSEAL 15 [hp_X]/1 g; POTASSIUM CARBONATE 15 [hp_X]/1 g; LYCOPODIUM CLAVATUM SPORE 15 [hp_X]/1 g; MAGNESIUM CHLORIDE 15 [hp_X]/1 g; DAPHNE MEZEREUM BARK 15 [hp_X]/1 g; STRYCHNOS NUX-VOMICA SEED 15 [hp_X]/1 g; PODOPHYLLUM 15 [hp_X]/1 g; KRAMERIA LAPPACEA ROOT 15 [hp_X]/1 g; SANICULA EUROPAEA LEAF 15 [hp_X]/1 g; SELENIUM 15 [hp_X]/1 g; SEPIA OFFICINALIS JUICE 15 [hp_X]/1 g; SILICON DIOXIDE 15 [hp_X]/1 g; TOBACCO LEAF 15 [hp_X]/1 g; VERATRUM ALBUM ROOT 15 [hp_X]/1 g; GRAPHITE 15 [hp_X]/1 g; IRIS VERSICOLOR ROOT 6 [hp_X]/1 g
INACTIVE INGREDIENTS: SUCROSE

Constipation 1723P

INDICATIONS AND USAGE SECTION

Formulated for associated symptoms such as difficult elimination, hard stools, pain, tenderness, pressure and irritability.

DOSAGE & ADMINISTRATION SECTION

Directions: Children, ages 0 to 11, give 3 pellets by mouth (ages 12 and up, give 6 pellets) as needed or a directed by a health professional. Under age 2, crush/dissolve pellets in purified water. Sensitive person begin with 1 pellet and gradually increase to full dose.

OTC - ACTIVE INGREDIENT SECTION

Equal parts of Echinacea 6x, Iris versicolor 6x, Phytolacca decandra 6x, Taraxacum officinale 6x, Abies nigra 15x, Aesculus hippocastanum 15x, Aloe 15x, Alumina 15x, Bryonia 15x, Carbo vegetabilis 15x, Chelidonium majus 15x, Collinsonia canadensis 15x, Graphites 15x, Hydrastis canadensis 15x, Kali carbonicum 15x, Lycopodium clavatum 15x, Magnesia muriatica 15x, Mezereum 15x, Nux vomica 15x, Podophyllum peltatum 15x, Rhamnus purshiana 15x, Sanicula 15x, Selenium metallicum 15x, Sepia 15x, Silicea 15x, Tabacum 15x, Veratrum album 15x, Zincum metallicum 15x.

OTC - PURPOSE SECTION

Formulated for associated symptoms such as difficult elimination, hard stools, pain, tenderness, pressure and irritability.

INACTIVE INGREDIENT SECTION

Gluten-free, non-GMO, organic beet-derived sucrose (lactose-free) pellets.

QUESTIONS SECTION

newtonlabs.net – Questions? 800.448.7256

Newton Laboratories, Inc. FDA Est # 1051203 - Conyers, GA 30013

WARNINGS SECTION

WARNINGS: Keep out of reach of children. Do not use if tamper-evident seal is broken or missing. If symptoms worsen or persist for more than a few days, consult a doctor. If pregnant or breast-feeding, ask a doctor before use.

OTC - PREGNANCY OR BREAST FEEDING SECTION

If pregnant or breast-feeding, ask a doctor before use.

OTC - KEEP OUT OF REACH OF CHILDREN SECTION

WARNINGS: Keep out of reach of children. Do not use if tamper-evident seal is broken or missing. If symptoms worsen or persist for more than a few days, consult a doctor. If pregnant or breast-feeding, ask a doctor before use.